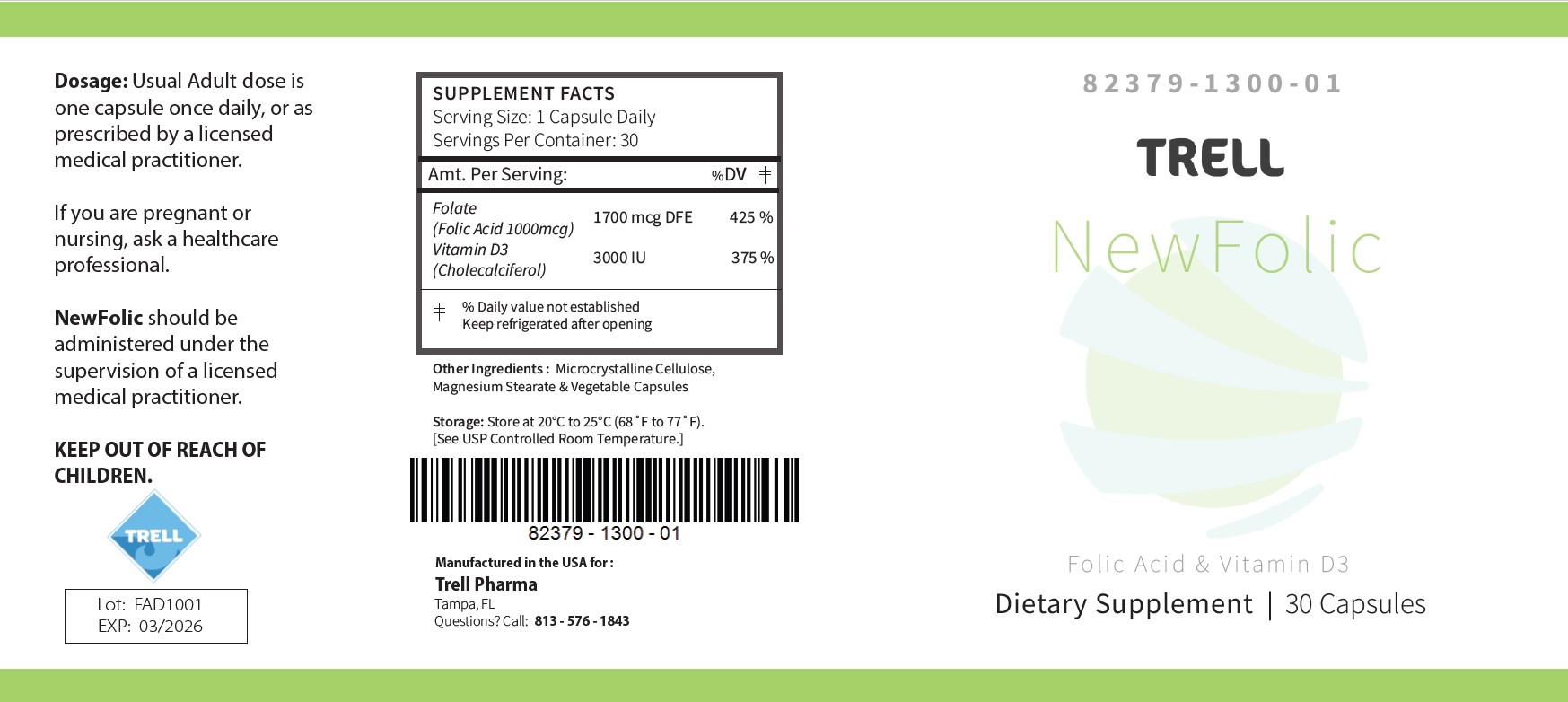 DRUG LABEL: NewFolic
NDC: 82379-1300 | Form: CAPSULE
Manufacturer: Trell Pharma
Category: other | Type: DIETARY SUPPLEMENT
Date: 20230921

ACTIVE INGREDIENTS: FOLIC ACID 1 mg/1 1; VITAMIN D 75 ug/1 1
INACTIVE INGREDIENTS: MICROCRYSTALLINE CELLULOSE; MAGNESIUM STEARATE

NewFolic

STATEMENT OF IDENTITY

NewFolic

Other Ingredients: Microcrystalline Cellulose, Magnesium Stearate & Vegatable Capsules

NewFolic is an orally administered prescription folate product for the dietary management of patients with unique nutritional needs requiring increased folate levels and Vitamin D supplementation due to Vitamin D deficiency.

NewFolic is manufactured in accordance with Current Good Manufacturing Practice for foods, using ingredients that have been approved by the U.S. Food and Drug Administration (FDA) as food additives or are Generally Recognized as Safe (GRAS) for their intended use.

DOSAGE

Usual Adult dose is one capsule once daily, or as prescribed by a licensed medical practitioner.
If you are pregnant or nursing, ask a healthcare professional.

NewFolic should be administered under the supervision of a licensed medical practitioner.

WARNINGS AND PRECAUTIONS

This product is contraindicated in patients with a known hypersensitivity to any of the ingredients.

NewFolic should only be used under the direction and supervision of a licensed medical practitioner. Use with caution in patients that may have a medical condition, are pregnant, lactating, trying to conceive, under the age of 18, or taking medications.

Each tablet contains:

Folic Acid ..........................................................................1700 mcg DFE

(Folic Acid 1000mcg)

Vitamin D3 (Cholecalciferol) ...................................... 75 mcg

(3000 IU)

Tell your doctor if you have: kidney problems, thyroid disease. This medication should be used as directed during pregnancy or while breast-feeding. Consult your doctor about the risks and benefits.

Folic Acid alone is improper therapy in the treatment of pernicious anemia and other megaloblastic anemias where Vitamin B12 is deficient. Folic acid in doses above 0.1 mg daily may obscure pernicious anemia in that hematologic remission can occur while neurological manifestations progress.

Allergic sensitization has been reported following both oral and parenteral administration of folic acid.

You should call your doctor for medical advice about serious adverse events. To report adverse side effects or to obtain product information, contact PureTek Corporation, at 1-813-576-1843.

KEEP OUT OF REACH OF CHILDREN

STORAGE AND HANDLING SECTION

Store at 20°-25°C (68°-77°F); excursions permitted to 15°-30°C (59°-86°F) [see USP Controlled Room Temperature].

Protect from heat, light and moisture.

Manufactured for Trell Pharma

Tampa, FL

Questions? Call: 813-576-1843

HEALTH CLAIM:

NewFolic is used for dietary management of patients with unique nutritional needs requiring increased folate levels, Vitamin D deficiency or are in need of Vitamin D supplementation and other nutritional supplementation.

NewFolic can be taken by women of childbearing age, pregnant women, and lactating and nonlactating mothers.